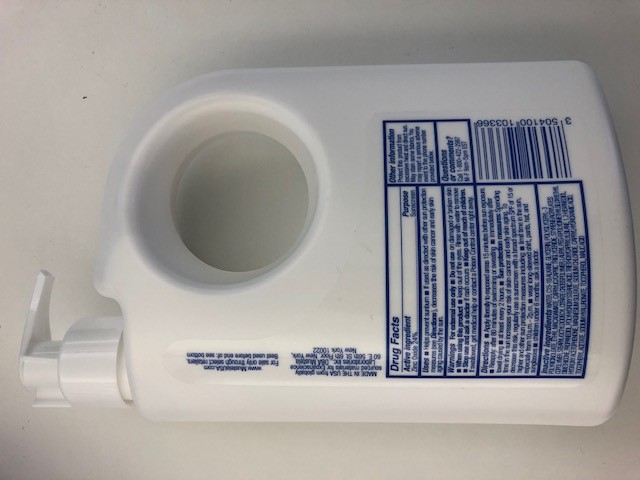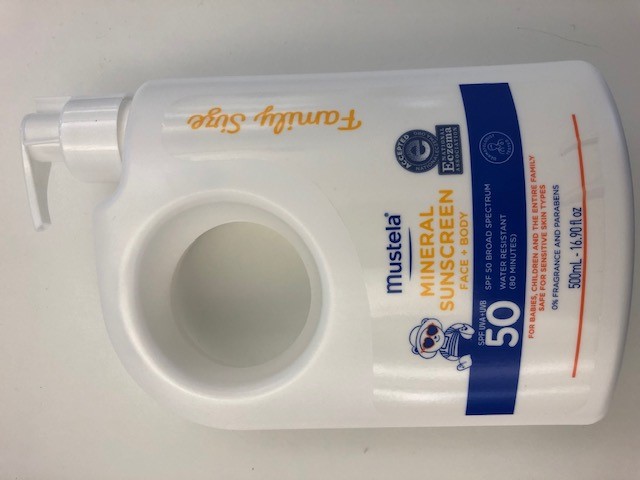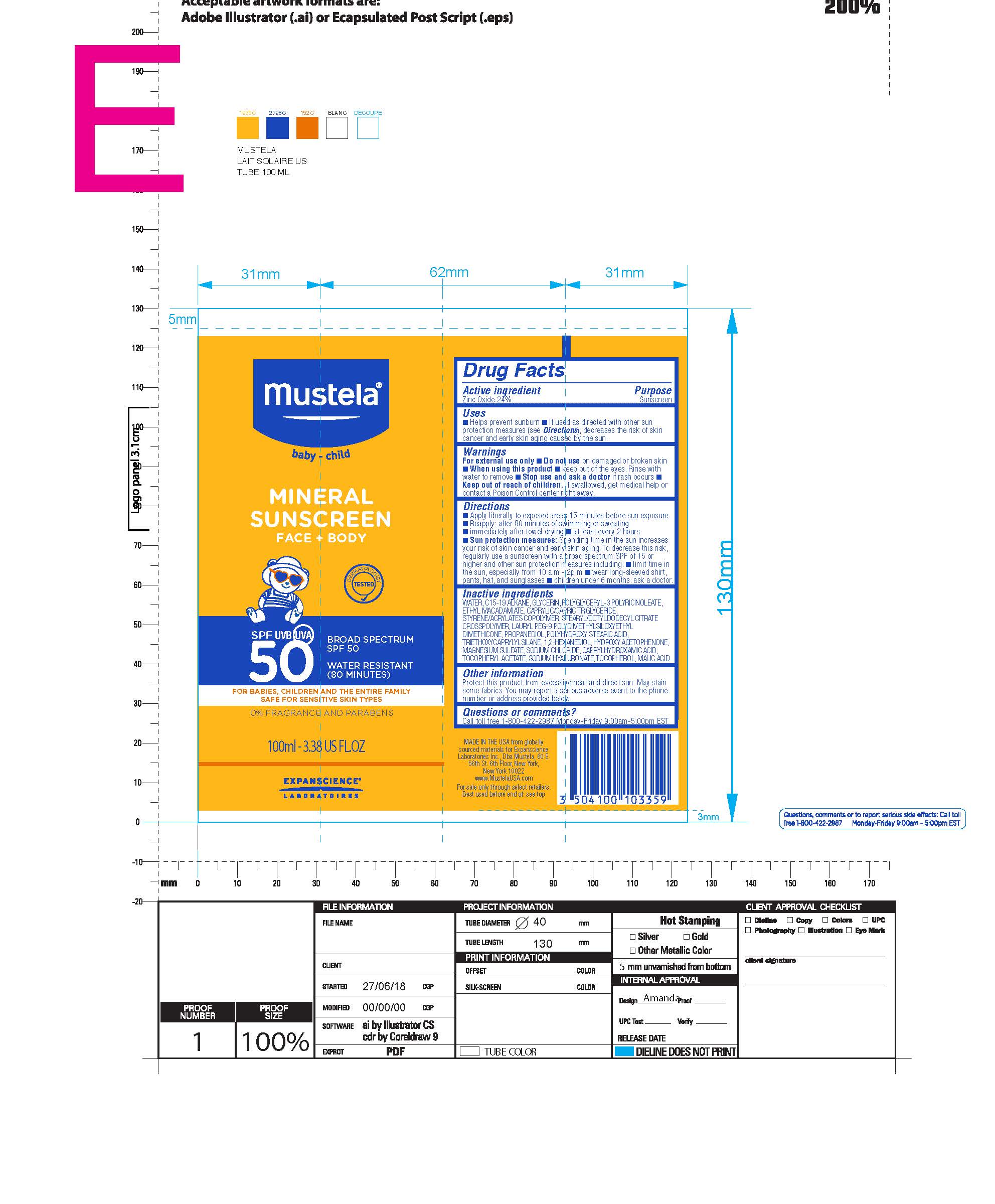 DRUG LABEL: Sunscreen
NDC: 61354-090 | Form: CREAM
Manufacturer: Oxygen development
Category: otc | Type: HUMAN OTC DRUG LABEL
Date: 20230210

ACTIVE INGREDIENTS: ZINC OXIDE 24 mg/100 mg
INACTIVE INGREDIENTS: WATER; BUTYL METHACRYLATE/METHYL METHACRYLATE/METHACRYLIC ACID/STYRENE CROSSPOLYMER; SODIUM CHLORIDE; GLYCERIN; TRIETHOXYCAPRYLYLSILANE; MAGNESIUM SULFATE, UNSPECIFIED; CAPRYLIC/CAPRIC/LAURIC TRIGLYCERIDE; STEARYL/OCTYLDODECYL CITRATE CROSSPOLYMER; LAURYL PEG-9 POLYDIMETHYLSILOXYETHYL DIMETHICONE; POLYHYDROXYSTEARIC ACID (2300 MW); C15-19 ALKANE; POLYGLYCERYL-3 RICINOLEATE; ETHYL MACADAMIATE; PROPANEDIOL; 1,2-HEXANEDIOL; HYDROXYACETOPHENONE

MUSTELA MINERAL SUNSCREEN FACE+BODY SPF50

Active Ingredient

Zinc Oxide 24%

Purpose

Sunscreen

Uses

Helps to prevent the sunburn. If used as directed with other sun protection measures (see Directions), decreases the risk of skin cancer and early skin aging caused by the sun.

Warnings

For external use only.

Do not use on damaged or broken skin.

When Using

When using this product keep out of the eyes. Rinse with water to remove.

Stop Use

Stop use and ask a doctor if rash occurs.

Keep out of reach of children. If swallowed, get medical help or contact a Poison Control center right away.

Directions

Apply liberally to exposed areas 15 minutes before sun exposure.Reapply: after 80 minutes of swimming or sweating. Immediately after towel drying. At least every 2 hours.Sun protection measures: Spending time in the sun increases your risk of skin cancer and early skin aging. To decrease this risk, regularly use a sunscreen with a broad spectrum SPF of 15 or higher and other sun protection measures including:
Limit time in the sun, expecially from 10 a.m. - 2 p.m.wear long-sleeved shirt, pants, hat and sunglasses children under 6 months: ask a doctor.

Inactive Ingredients

WATER, C15-19 ALKANE, GLYCERIN, POLYGLYCERYL-3 POLYRICINOLEATE, ETHYL MACADAMIATE, CAPRYLIC/CAPRIC TRIGLYCERIDE, STYRENE/ACRYLATES COPOLYMER, STEARYL/OCTYLDODECYL CITRATE CROSSPOLYMER, LAURYL PEG-9 POLYDIMETHYLSILOXYETHYL DIMETHICONE, PROPANEDIOL, POLYHYDROXYSTEARIC ACID, TRIETHOXYCAPRYLYLSILANE, 1,2-HEXANEDIOL, HYDROXYACETOPHENONE, MAGNESIUM SULFATE, SODIUM CHLORIDE, CAPRYLHYDROXAMIC ACID, TOCOPHERYL ACETATE, SODIUM HYALURONATE, TOCOPHEROL, MALIC ACID

Other Information

Protect this product from excessive heat and direct sun. May stain some fabrics. You may report a serious adverse event to the phone number or address provided below.

Questions or Comments?

Call toll free 1-800-422-2987 Monday-Friday 9:00am-5:00pm EST

Primary Package 500ml

500ml, 61354-070-02